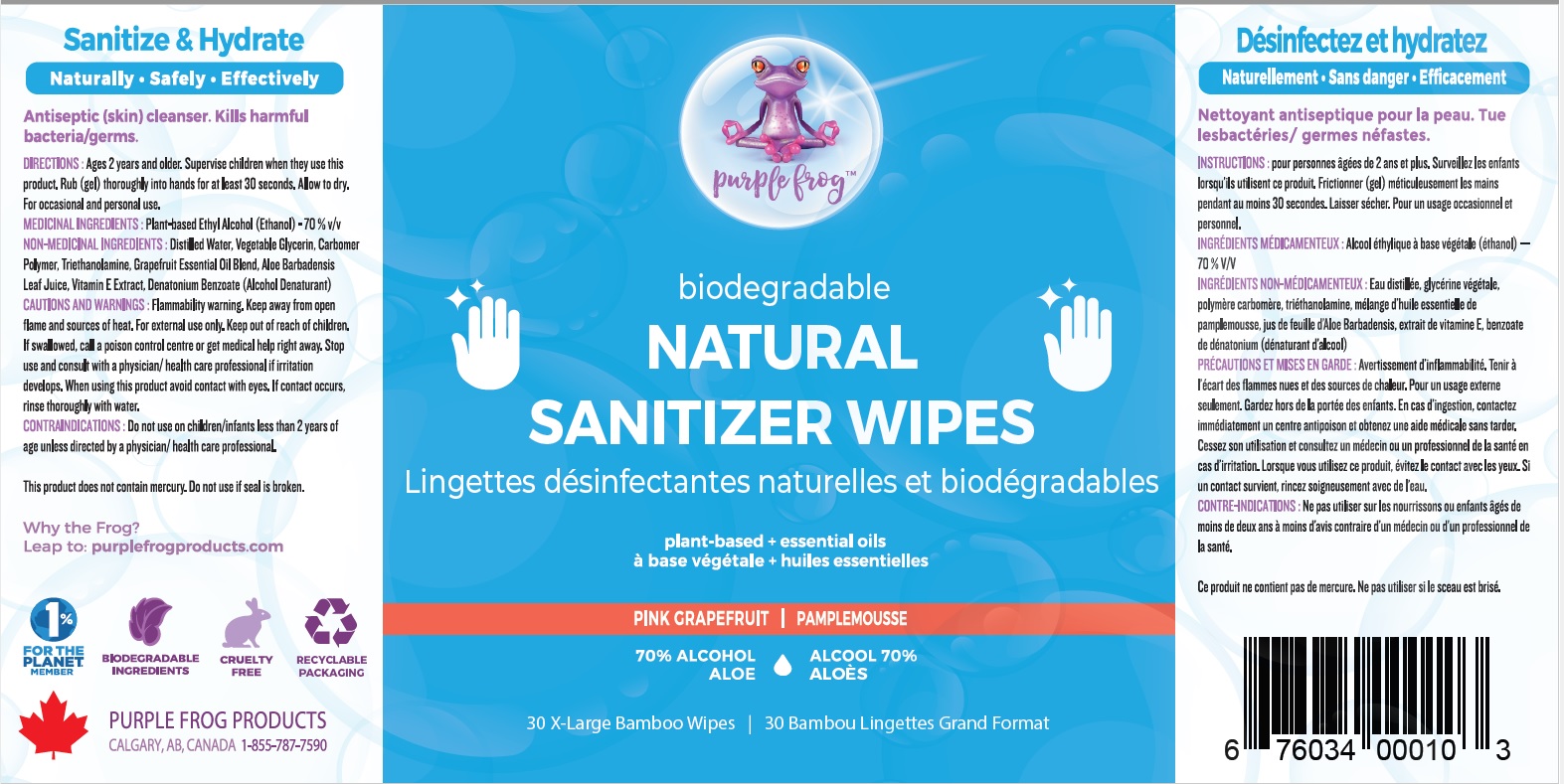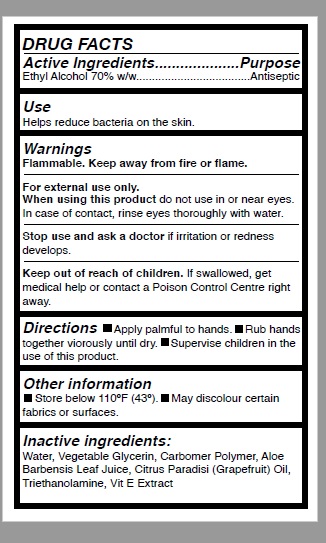 DRUG LABEL: Ethyl alcohol wet wipes
NDC: 80382-003 | Form: CLOTH
Manufacturer: Natural Distributions Ltd. o/a Purple Frog Products Suite
Category: otc | Type: HUMAN OTC DRUG LABEL
Date: 20201118

ACTIVE INGREDIENTS: ALCOHOL 0.7 mL/1 1
INACTIVE INGREDIENTS: WATER; GLYCERIN; ALOE VERA LEAF; CARBOMER COPOLYMER TYPE A; .ALPHA.-TOCOPHEROL ACETATE; GRAPEFRUIT OIL; DENATONIUM BENZOATE

Purple Frog Ethyl alcohol wet wipes

Active Ingredient

Ethyl Alcohol (70.00% V/V)

Purpose

Antiseptic

Uses

- For hand-washing to decrease bacteria on skin

Warnings

Flammable. Keep away from heat and flame.
For External use only.

Do not use

in eyes. In case of contact, rinse thoroughly with water.

Stop use & ask doctor

if rash/redness or irritation appears/develops and persist for more than 72 hours.

Keep out of reach from children

except under adult supervision. If swallowed, get medical help or contact a Poison Control Center

Directions

- Slowly peel back label and use one wipe. Reseal, keep closed to prevent evaporation.
- Thoroughly wipe hands, allow to dry without washing.
- Discard after single use

Other information

- Do not flush down toilet.
- Keep away from sunlight. Store at room temperature 20°-25°Celsius (68°-77° Fahrenheit)
- May discolor certain fabrics

Inactive Ingredients

Distilled Water, Vegetable Glycerin, Carbomer, Grapefruit Essential Oil Blend, Aloe Barbadensis Leaf Juice, Denatonium Benzoate.